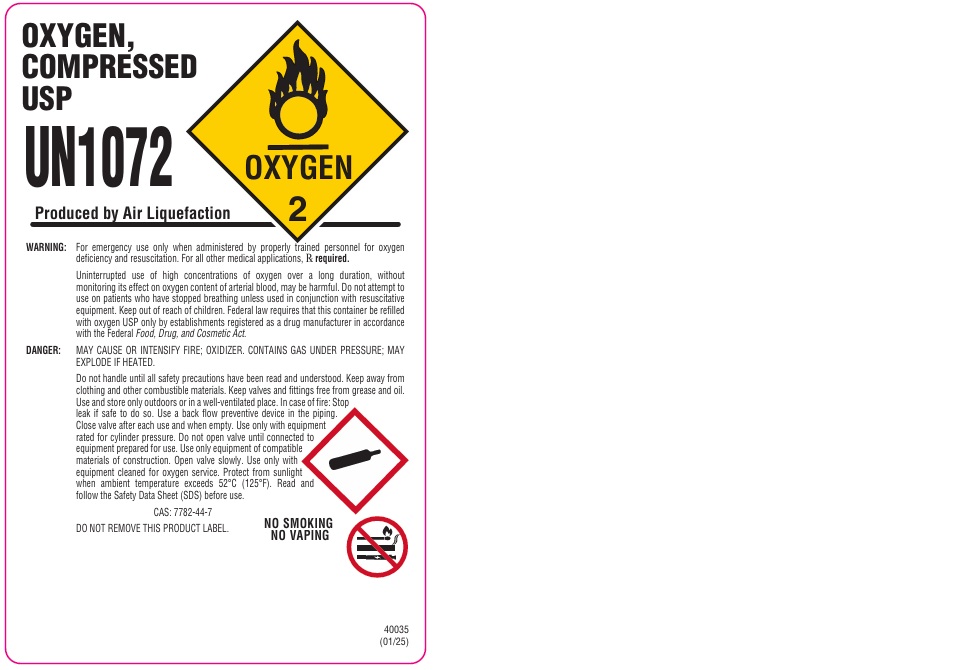 DRUG LABEL: Oxygen, Compressed U.S.P.
NDC: 64069-4112 | Form: GAS
Manufacturer: Techgas Inc.
Category: animal | Type: PRESCRIPTION ANIMAL DRUG LABEL
Date: 20251210

ACTIVE INGREDIENTS: OXYGEN 1 L/1 L

OXYGEN, COMPRESSED U.S.P.

PACKAGE LABEL

OXYGEN, COMPRESSED USP
UN1072
Produced by Air Liquefaction
WARNING: For emergency use only when administered by properly trained personnel for oxygen deficiency and resuscitation. For all other medical applications, Rx required.
Uninterrupted use of high concentrations of oxygen over a long duration, without monitoring its effect on oxygen content of arterial blood, may be harmful. Do not attempt to use on patients who have stopped breathing unless used in conjunction with resuscitative equipment. Keep out of reach of children. Federal law requires that this container be refilled with oxygen USP only by establishments registered as a drug manufacturer in accordance with the Federal Food, Drug, and Cosmetic Act.
DANGER: MAY CAUSE OR INTENSIFY FIRE; OXIDIZER. CONTAINS GAS UNDER PRESSURE; MAY EXPLODE IF HEATED.
Do not handle until all safety precautions have been read and understood. Keep away from clothing and other combustible materials. Keep valves and fittings free from grease and oil. Use and store only outdoors or in a well-ventilated place. In case of fire: Stop leak if safe to do so. Use a back flow preventive device in the piping. Close valve after each use and when empty. Use only with equipment rated for cylinder pressure. Do not open valve until connected to equipment prepared for use. Use only equipment of compatible materials of construction. Open valve slowly. Use only with equipment cleaned for oxygen service. Protect from sunlight when ambient temperature exceeds 52 C (125 F). Read and follow the Safety Data Sheet (SDS) before use.
CAS: 7782-44-7
DO NOT REMOVE THIS PRODUCT LABEL.
NO SMOKING
NO VAPING